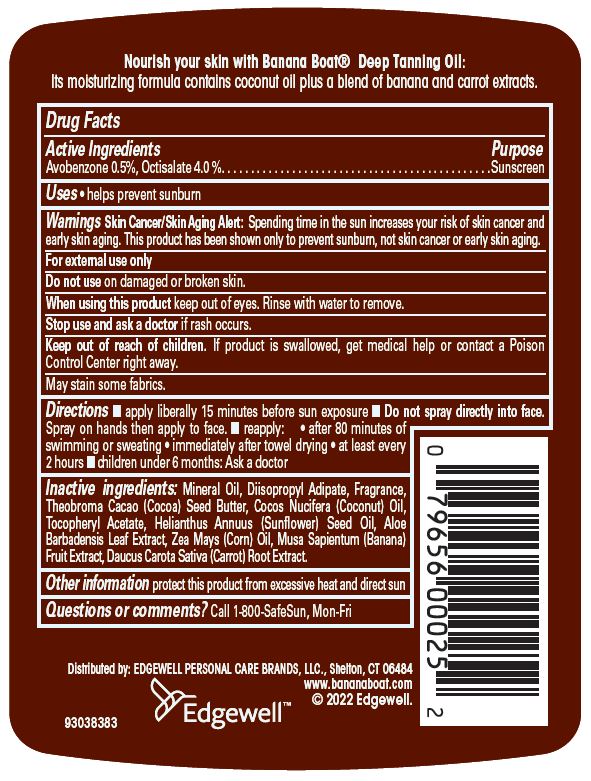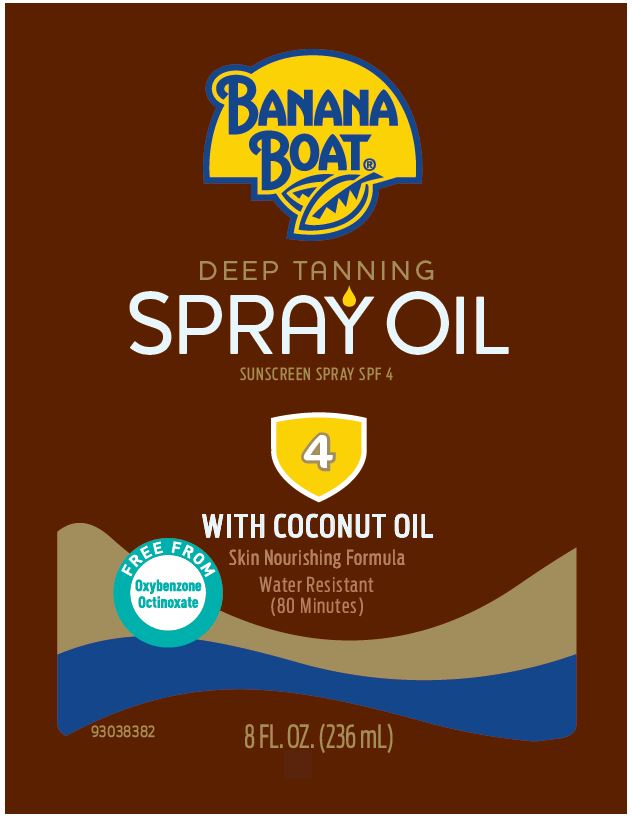 DRUG LABEL: Banana Boat Deep Tanning Sunscreen SPF 4
NDC: 63354-649 | Form: OIL
Manufacturer: Edgewell Personal Care Brands LLC
Category: otc | Type: HUMAN OTC DRUG LABEL
Date: 20231109

ACTIVE INGREDIENTS: AVOBENZONE 0.5 g/100 g; OCTISALATE 4 g/100 g
INACTIVE INGREDIENTS: COCOA BUTTER; SUNFLOWER OIL; CORN OIL; BANANA; MINERAL OIL; DIISOPROPYL ADIPATE; CARROT; COCONUT OIL; .ALPHA.-TOCOPHEROL ACETATE; ALOE VERA LEAF

Active Ingredients

Avobenzone 0.5%, Octisalate 4.0%

Purpose

Sunscreen

Uses

• helps prevent sunburn

Warnings

Skin Cancer/Skin Aging Alert: Spending time in the sun increases your risk of skin cancer and early skin aging. This product has been shown only to prevent sunburn, not skin cancer or early skin aging.

For external use only

May stain some fabrics.

Do not use

on damaged or broken skin

When using this product

keep out of eyes. Rinse with water to remove.

Stop use and ask a doctor

if rash occurs

Keep out of reach of children

If product is swallowed, get medical help or contact a Poison Control Center right away.

Directions

• apply liberally 15 minutes before sun exposure • Do not spray directly into face. Spray on hands then apply to face. • reapply: • after 80 minutes of swimming or sweating • immediately after towel drying • at least every 2 hours • children under 6 months: Ask a doctor

Inactive ingredients

Mineral Oil, Diisopropyl Adipate, Fragrance, Theobroma Cacao (Cocoa) Seed Butter, Cocos Nucifera (Coconut) Oil, Tocopheryl Acetate, Helianthus Annuus (Sunflower) Seed Oil, Aloe Barbadensis Leaf Extract, Zea Mays (Corn) Oil, Musa Sapientum (Banana) Fruit Extract, Daucus Carota Sativa (Carrot) Root Extract

Other information

protect this product from excessive heat and direct sun

Questions or comments?

Call 1-800-SafeSun, Mon-Fri

Primary Display Panel

BANANA
BOAT®
DEEP TANNING
SPRAY OIL
SUNSCREEN SPRAY SPF 4
4
WITH COCONUT OIL
FREE FROM
Oxybenzone
Octinoxate
Skin Nourishing Formula
Water Resistant
(80 Minutes)
8 FL. OZ. (236 mL)